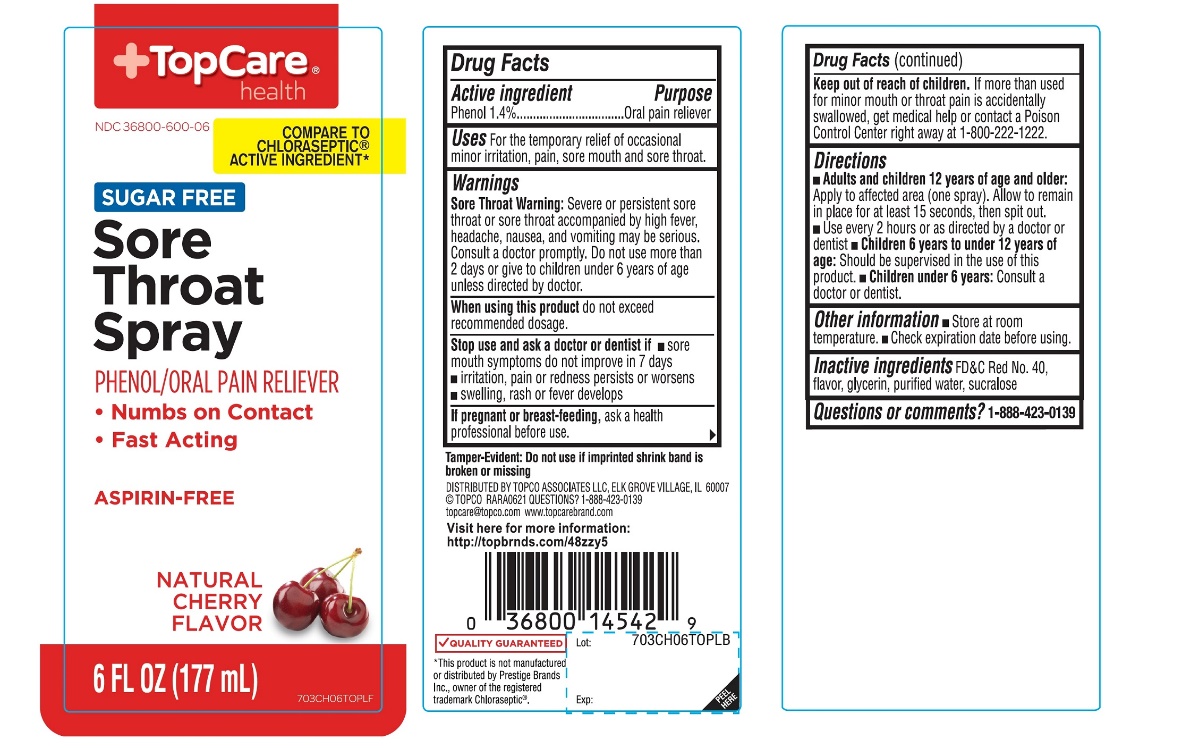 DRUG LABEL: TopCare

NDC: 36800-600 | Form: SPRAY
Manufacturer: TOPCO ASSOCIATES, LLC
Category: otc | Type: HUMAN OTC DRUG LABEL
Date: 20251110

ACTIVE INGREDIENTS: PHENOL 1.4 g/100 mL
INACTIVE INGREDIENTS: FD&C RED NO. 40; GLYCERIN; WATER; SUCRALOSE

TopCare SUGAR-FREE Sore Throat Spray

Active ingredient

Phenol 1.4%

Purpose

Oral Anesthetic/Analgesic

Uses

For the temporarily relief of occasional minor irritation, pain, sore mouth and sore throat.

Warnings

Sore throat warning:Severe or persistent sore throat or sore throat accompanied by high fever, headache, nausea, and vomiting may be serious. Consult a doctor promptly. Do not use more than 2 days or administer to children under 6 years of age unless directed by a doctor.

When using this product,

do not exceed recommended dosage.

Stop use and ask a dentist or doctor if

- sore mouth symptoms do not improve in 7 days
- irritation, pain or redness persists or worsens
- swelling, rash or fever develops

If pregnant or breast-feeding,

ask a doctor before use.

Keep out of reach of children.

In case of overdose or accidental poisoning,get medical help or contact a Poison Control Center right away (1-800-222-1222).

Directions

- Adults and children 12 years of age and older
  - apply to affected area (one spray)
  - allow to remain in place for at least 15 seconds, then spit out
  - use every 2 hours as directed by a doctor or dentist
- Children under 12 years of age: should be supervised in the use of this product
- Children under 6 years of age, Ask a doctor or dentist

Other information

- Store at room temperature.
- Check expiration date before using.

Inactive ingredients

FD&C Red No. 40, flavor, glycerin, purified water, sucralose.

Questions or comments?

1-888-423-0139

Principal Display Panel

TopCare®health™

COMPARE TO CHLORASEPTIC® ACTIVE INGREDIENT*

NDC# 36800-600-06

SUGAR-FREE

Sore Throat Spray

PHENOL/ORAL ANESTHETIC

- Works on Contact
- Relieves Sore Throat Pain
- Fast Acting

ASPIRIN-FREE

ALCOHOL-FREE

CHERRY FLAVOR

6 FL OZ (177 mL)

OUR PHARMACIST RECOMMEND

QUALITY GUARANTEED

*This product is not manufactured or distributed by Prestige Brands, Co., distributor of Chloraseptic®.

TAMPER EVIDENT: DO NOT USE IF IMPRINTED SHRINK BAND IS BROKEN OR MISSING

DISTRIBUTED BY

TOPCO ASSOCIATES LLC,

ELK GROVE VILLAGE, IL 6007

TOPCO RARA1217

QUESTIONS? 1-888-423-0139

topcare@topco.comwww.topcarebrand.com